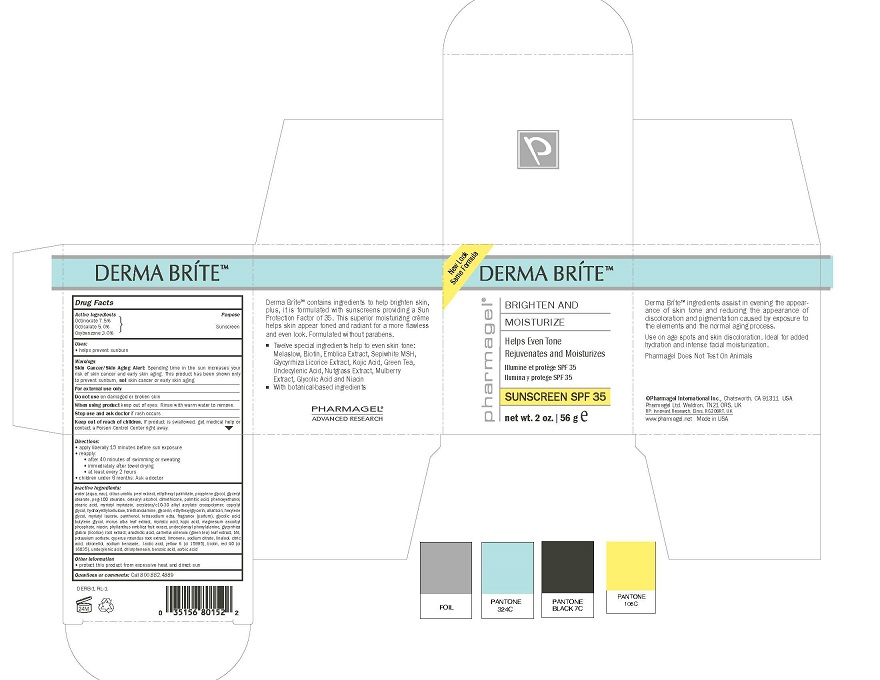 DRUG LABEL: DERMA BRITE

NDC: 67879-308 | Form: CREAM
Manufacturer: PHARMAGEL INTERNATIONAL INC
Category: otc | Type: HUMAN OTC DRUG LABEL
Date: 20240813

ACTIVE INGREDIENTS: OCTINOXATE 7.5 g/100 g; OCTISALATE 5 g/100 g; OXYBENZONE 3 g/100 g
INACTIVE INGREDIENTS: WATER; TANGERINE PEEL; ETHYLHEXYL PALMITATE; PROPYLENE GLYCOL; GLYCERYL MONOSTEARATE; PEG-100 STEARATE; CETOSTEARYL ALCOHOL; DIMETHICONE; PALMITIC ACID; PHENOXYETHANOL; STEARIC ACID; MYRISTYL MYRISTATE; CARBOMER COPOLYMER TYPE A (ALLYL PENTAERYTHRITOL CROSSLINKED); CAPRYLYL GLYCOL; HYDROXYETHYL CELLULOSE (100 MPA.S AT 2%); TROLAMINE; GLYCERIN; ETHYLHEXYLGLYCERIN; ALLANTOIN; HEXYLENE GLYCOL; MYRISTYL LAURATE; PANTHENOL; EDETATE SODIUM; GLYCOLIC ACID; BUTYLENE GLYCOL; MORUS ALBA LEAF; MYRISTIC ACID; KOJIC ACID; MAGNESIUM ASCORBYL PHOSPHATE; NIACIN; PHYLLANTHUS EMBLICA FRUIT; UNDECYLENOYL PHENYLALANINE; GLYCYRRHIZA GLABRA; ARACHIDIC ACID; GREEN TEA LEAF; BUTYLATED HYDROXYTOLUENE; POTASSIUM SORBATE; CYPERUS ROTUNDUS ROOT; LIMONENE, (+)-; SODIUM CITRATE; LINALOOL, (+)-; ANHYDROUS CITRIC ACID; .BETA.-CITRONELLOL, (+/-)-; SODIUM BENZOATE; LACTIC ACID; FD&C YELLOW NO. 6; BIOTIN; FD&C RED NO. 40; UNDECYLENIC ACID; CHLORPHENESIN; BENZOIC ACID; SORBIC ACID

PHARMAGEL - DERMA BRITE (67879-308)

ACTIVE INGREDIENTS

Octinoxate 7.5%

Octisalate 5.0%

Oxybenzone 3.0%

PURPOSE

Sunscreen

USES

- helps prevent sunburn
- if used as directed with other sun protection measures (see Directions), decreases the risk of skin cancer and early skin aging caused by the sun

WARNINGS

For external use only.

Do not use on damaged or broken skin.

When using product keep out of eyes. Rinse with warm water to remove.

Stop use and ask doctor if rash occurs

Keep out of reach of children. If product is swallowed, get medical help or contact a Poison Control Center right away.

DIRECTIONS

• apply liberally 15 minutes before sun exposure

• reapply:
• after 40 minutes of swimming or sweating.

• immediately after towel drying
• at least every 2 hours

• Sun Protection Measures. Spending time in the sun increases your risk of skin cancer and early aging. To decrease this risk, regularly use a sunscreen with a broad spectrum SPF of 15 or higher and other sun protection measures including:
• limit time in the sun, especially from 10 a.m. - 2 p.m.
• wear long-sleeve shirts, pants, hats and sunglasses
• children under 6 months: Ask a doctor

INACTIVE INGREDIENTS:

water (aqua, eau), citrus unshiu peel extract, ethylhexyl palmitate, propylene glycol, glyceryl stearate, peg-100 stearate, cetearyl alcohol, dimethicone, palmitic acid, phenoxyethanol, stearic acid, myristyl myristate, acrylates/c10-30 alkyl acrylate crosspolymer, caprylyl glycol, hydroxyethylcellulose, triethanolamine, glycerin, ethylhexylglycerin, allantoin, hexylene glycol, myristyl laurate, panthenol, tetrasodium edta, fragrance (parfum), glycolic acid, butylene glycol, morus alba leaf extract, myristic acid, kojic acid, magnesium ascorbyl phosphate, niacin, phyllanthus emblica fruit exract, undecylenoyl phenylalanine, glycyrrhiza glabra (licorice) root extract, arachidic acid, camellia sinensis (green tea) leaf extract, bht, potassium sorbate, cyperus rotundus root extract, limonene, sodium citrate, linalool, citric acid, citronellol, sodium benzoate, lactic acid, yellow 6 (ci 15985), biotin, red 40 (ci 16035), undecylenic acid, chlorphenesin, benzoic acid, sorbic acid